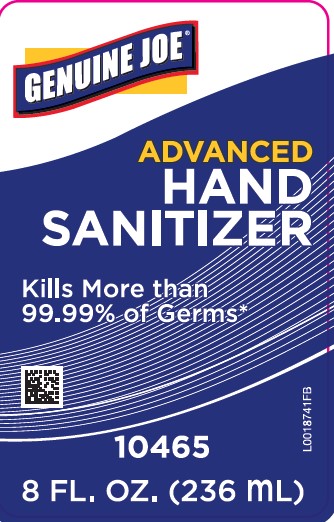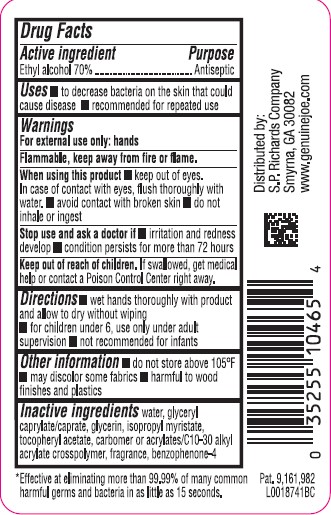 DRUG LABEL: Antibacterial Hand Sanitizer
NDC: 62832-370 | Form: GEL
Manufacturer: S. P. Richards Company
Category: otc | Type: HUMAN OTC DRUG LABEL
Date: 20260218

ACTIVE INGREDIENTS: ALCOHOL 70 mL/100 mL
INACTIVE INGREDIENTS: WATER; GLYCERYL CAPRYLATE/CAPRATE; GLYCERIN; ISOPROPYL MYRISTATE; .ALPHA.-TOCOPHEROL ACETATE; CARBOMER HOMOPOLYMER, UNSPECIFIED TYPE; CARBOMER INTERPOLYMER TYPE A (ALLYL SUCROSE CROSSLINKED); SULISOBENZONE

Genuine Joe 370.001/370AE rev 1
Advanced Hand Sanitizer

Active ingredient

Ethyl alcohol 70%

Purpose

Antiseptic

Uses

- to decrease bacteria on the skin that could cause disease
- recommended for repeated use

Warnings

For external use only: hands

Flammable, keep away from heat and flame.

When using this product

- keep out of eyes. In case of contact with eyes, flush thoroughly with water.
- avoid contact with broken skin
- do not inhale or ingest

Stop use and ask a doctor if

- irritation and redness develop
- condition persists for more than 72 hours

Keep out of reach of children

If swallowed, get medical help or contact a Poison Control Center right away.

Directions

- wet hands thoroghly with product and allow to dry without wiping
- for children under 6, use only under adult supervision
- not recommended for infants

Other information

- do not store above 105⁰ F
- may discolor some fabrics
- harmful to wood finishes and plastics

Inactive ingredients

water, glyceryl caprylate/caprate, glycerin, isopropyl myristate, tocopheryl acetate, carbomer or acrylates/C10-30 alkyl acrylate crosspolymer, fragrance, benzophenone-4

Claims

*Effective at eliminating more than 99.99% of many common harmful germs and bacteria in as little as 15 seconds.

Adverse Reaction

Distributed by

S.P. Richards Company

Smyrna, GA 30082

www.genuinejoe.com

Pat. 9,161,982

Principal display panel

GENUINE JOE®

Advanced Hand Sanitizer

Kills more than 99.99% of germs*

10565

8 FL. OZ. (236 mL)